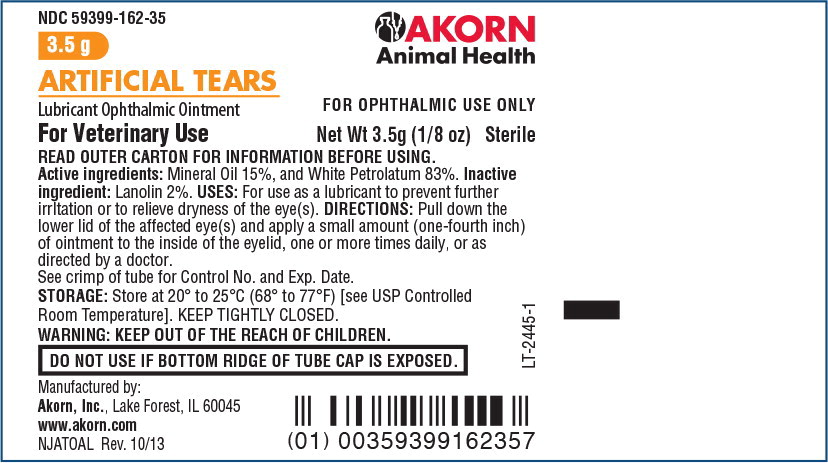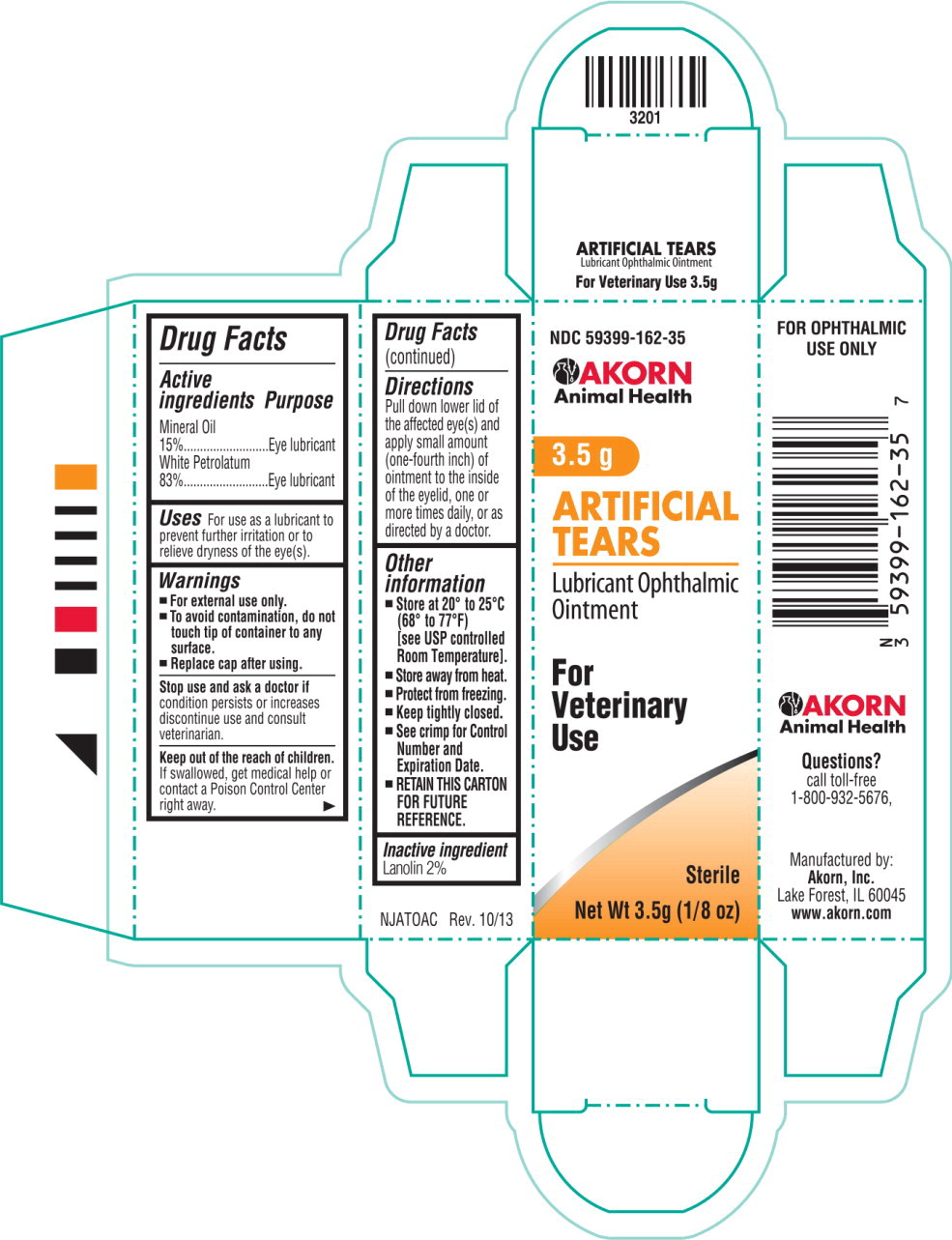 DRUG LABEL: Artificial Tears
NDC: 59399-162 | Form: OINTMENT
Manufacturer: Akorn
Category: animal | Type: OTC ANIMAL DRUG LABEL
Date: 20221103

ACTIVE INGREDIENTS: Mineral Oil 150 mg/1 g; Petrolatum 830 mg/1 g
INACTIVE INGREDIENTS: Lanolin

Drug Facts

Active ingredients

Mineral Oil 15%

White Petrolatum 83%

Purpose

Eye lubricant

Eye lubricant

Uses

For use as a lubricant to prevent further irritation or to relieve dryness of the eye(s).

Warnings

- For external use only.
- To avoid contamination, do not touch tip of container to any surface.
- Replace cap after using.

Stop use and ask a doctor if condition persists or increases discontinue use and consult veterinarian.

KEEP OUT OF REACH OF CHILDREN

Keep out of the reach of children. If swallowed, get medical help or contact a Poison Control Center right away.

Directions

Pull down lower lid of the affected eye(s) and apply small amount (one-fourth inch) of ointment to the inside of the eyelid, one or more times daily, or as directed by a doctor.

Other information

- Store at 20° to 25°C (68° to 77°F)
  [see USP controlled Room Temperature].
- Store away from heat.
- Protect from freezing.
- Keep tightly closed.
- See crimp for Control Number and Expiration Date.
- RETAIN THIS CARTON FOR FUTURE REFERENCE.

Inactive ingredient

Lanolin 2%

Principal Display Panel Text for Container Label:

NDC 59399-162-35 Akorn Animal Health Logo

3.5 g

ARTIFICIAL TEARS

Lubricant Ophthalmic Ointment FOR OPHTHALMIC USE ONLY

For Veterinary Use Net Wt 3.5g (1/8 oz) Sterile

Principal Display Panel Text for Carton Label:

NDC 59399-162-35

Akorn Animal Health Logo

3.5 g

ARTIFICIAL

TEARS

Lubricant Ophthalmic

Ointment

For

Veterinary

Use

Sterile

Net Wt 3.5g (1/8 oz)